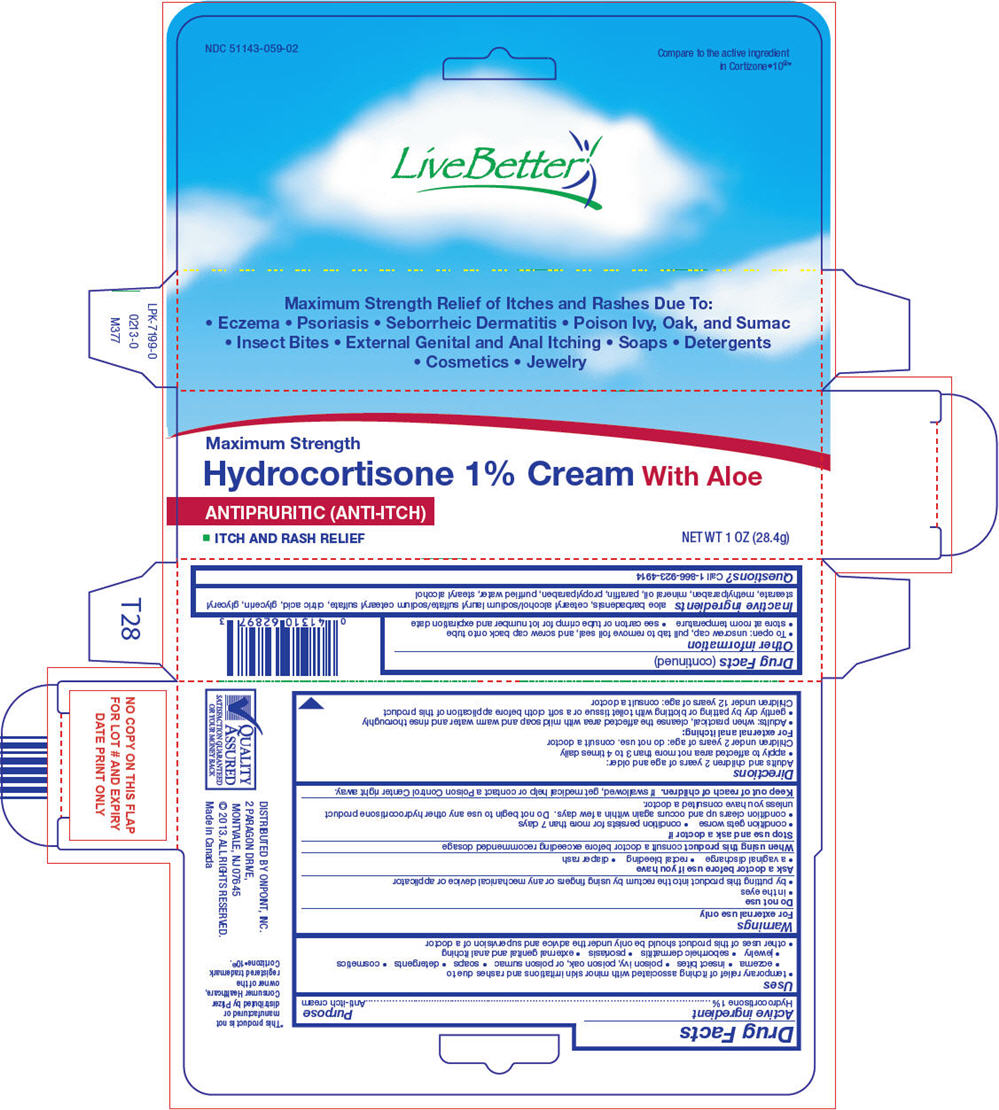 DRUG LABEL: Live Better

NDC: 51143-059 | Form: CREAM
Manufacturer: The Great Atlantic & Pacific Tea Company
Category: otc | Type: HUMAN OTC DRUG LABEL
Date: 20250710

ACTIVE INGREDIENTS: HYDROCORTISONE 1 g/100 g
INACTIVE INGREDIENTS: PROPYLPARABEN; WATER; STEARYL ALCOHOL; CETOSTEARYL ALCOHOL; SODIUM LAURYL SULFATE; SODIUM CETOSTEARYL SULFATE; CITRIC ACID MONOHYDRATE; GLYCERIN; GLYCERYL MONOSTEARATE; METHYLPARABEN; MINERAL OIL; PARAFFIN

Live Better
Hydrocortisone with Aloe

Drug Facts

Active ingredient

Hydrocortisone 1%

Purpose

Anti-itch cream

Uses

- temporary relief of itching associated with minor skin irritations and rashes due to
  - eczema
  - insect bites
  - poison ivy, poison oak, or poison sumac
  - soaps
  - detergents
  - cosmetics
  - jewelry
  - seborrheic dermatitis
  - psoriasis
  - external genital and anal itching
- other uses of this product should be only under the advice and supervision of a doctor

Warnings

For external use only

Do not use

- in the eyes
- by putting this product into the rectum by using fingers or any mechanical device or applicator

Ask a doctor before use if you have

- a vaginal discharge
- rectal bleeding
- diaper rash

WHEN USING

When using this productconsult a doctor before exceeding recommended dosage

Stop use and ask a doctor if

- condition gets worse
- condition persists for more than 7 days
- condition clears up and occurs again within a few days. Do not begin to use any other hydrocortisone product unless you have consulted a doctor.

Keep out of reach of children.If swallowed, get medical help or contact a Poison Control Center right away.

Directions

Adults and children 2 years of age and older:

- apply to affected area not more than 3 to 4 times daily

Children under 2 years of age: do not use. consult a doctor

For external anal itching

- Adults: when practical, cleanse the affected area with mild soap and warm water and rinse thoroughly
- gently dry by patting or blotting with toilet tissue or a soft cloth before application of this product

Children under 12 years of age: consult a doctor

Other information

- To open: unscrew cap, pull tab to remove foil seal, and screw cap back onto tube
- store at room temperature
- see carton or tube crimp for lot number and expiration date

Inactive ingredients

aloe barbadensis, cetearyl alcohol/sodium lauryl sulfate/sodium cetearyl sulfate, citric acid, glycerin, glyceryl stearate, methylparaben, mineral oil, paraffin, propylparaben, purified water, stearyl alcohol

Questions?

Call 1-866-923-4914

DISTRIBUTED BY ONPOINT, INC.
2 PARAGON DRIVE,
MONTVALE, NJ 07645

PRINCIPAL DISPLAY PANEL - 28.4 g Tube Carton

Maximum Strength

Hydrocortisone 1% Cream With Aloe

ANTIPRURITIC (ANTI-ITCH)

- ITCH AND RASH RELIEF

NET WT 1 OZ (28.4g)